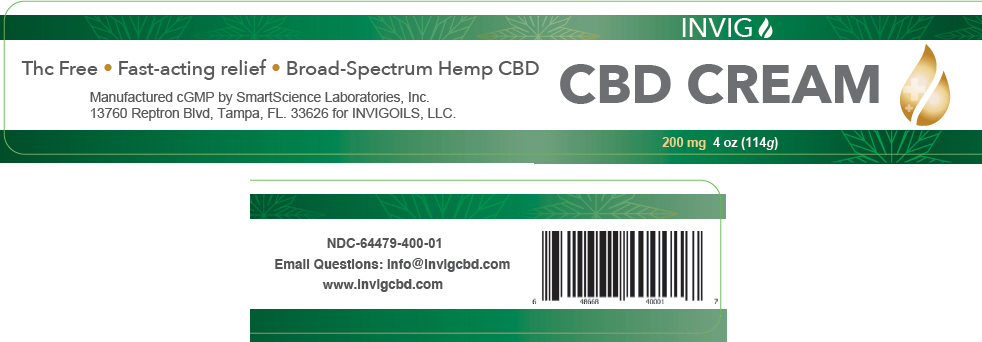 DRUG LABEL: CBD
NDC: 64479-400 | Form: CREAM
Manufacturer: SmartScience Laboratories, Inc.
Category: otc | Type: HUMAN OTC DRUG LABEL
Date: 20200210

ACTIVE INGREDIENTS: CAMPHOR (SYNTHETIC) 5 mg/100 g
INACTIVE INGREDIENTS: Methyl Glucose Sesquistearate; CARBOMER INTERPOLYMER TYPE A (ALLYL SUCROSE CROSSLINKED); Alkyl (C12-15) Benzoate; ALOE VERA LEAF; ARNICA MONTANA; CALCITRIOL; CHONDROITIN SULFATE (SHARK); Diazolidinyl Urea; Iodopropynyl Butylcarbamate; Dimethicone; EDETATE DISODIUM ANHYDROUS; PANTHENOL; .ALPHA.-TOCOPHEROL ACETATE; Escin; GLUCOSAMINE SULFATE POTASSIUM CHLORIDE; Glycerin; GLYCERYL MONOSTEARATE; HYPROMELLOSE, UNSPECIFIED; Methyl Gluceth-20; Peppermint Oil; Potassium Hydroxide; WATER; Shea Butter; Sorbitan Monolaurate; Trolamine Salicylate; Cannabidiol

CBD Cream

Drug Facts

Active Ingredient

Camphor (5.0%)

Purpose

External Analgesic

Uses

Temporarily relieves foot, ankle and leg pain associated with:

- arthritis
- muscle aches
- muscle strains
- joint pain

Directions

Use only as directed

- Do not use on children under 12 years of age.
- Apply onto affected area no more than four times daily.

Warnings

For external use only: Flammable: Keep away from excessive heat or open flame.

- Ask a doctor before use if you have sensitive skin or if you are taking any blood thinners.

When using this product

Do not use on wounds or irritated skin

- Do not bandage tightly or use with a heating pad
- Wash hands after use with cool water

PREGNANCY OR BREAST FEEDING

- If pregnant or breast feeding, ask a health professional before use

- Keep out of reach of children. If accidentally swallowed, contact a doctor or poison control center immediately

- Stop use and ask a doctor if condition worsens or if pain persists for more than 7 days, or clears up, then reoccurs within a few days.

Inactive Ingredients

Acrylate/C10-30 Alkyl Acrylate Crosspolymer, Aescin (Horse Chestnut Extract), Aloe Vera, Arnica Montana Extract, C12-15 Alkyl Benzoate, Chondroitin Sulfate, Diazodinyl Urea, Dimethicone, Disodium EDTA, dl Panthenol, Fructoborate, Cannabis Sativa Oil (Hemp Derived), Glucosamine Sulfate, Glycerin, Glycerol Stearate, Hydroxypropyl methylcellulose, Iodopropynyl Butylcarbamate, Methyl Gluceth-20, Methyl Glucose Sesquistearate, Peppermint Oil, Polysorbate 20, Potassium Carbomer, Purified Water, Shea Butter, Tocopheryl Acetate, Trolamine Salicylate

Other Information

Questions or comments? Email info@invigcbd.com.

Store in a cool dry place with the cap tightly closed. Note: Because this product contains natural ingredients, color may vary.

Manufactured cGMP by Smart Science Labs, 13760
Reptron Blvd Tampa, FL. 33626

PRINCIPAL DISPLAY PANEL - 114 g Jar Label

INVIG

CBD CREAM

200 mg 4 oz (114g)